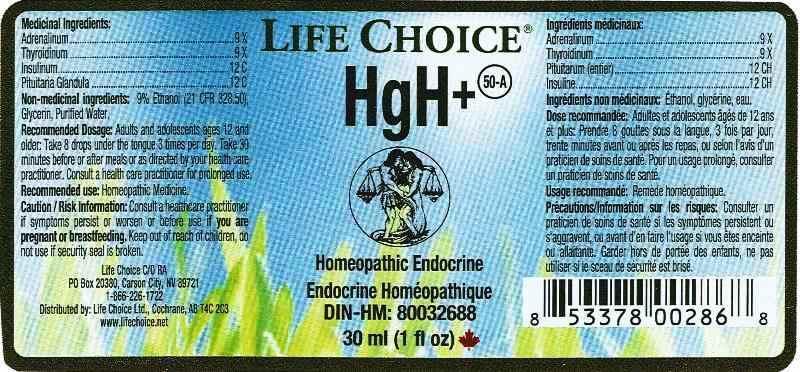 DRUG LABEL: HGH Plus
NDC: 55856-0003 | Form: LIQUID
Manufacturer: Life Choice Ltd.
Category: homeopathic | Type: HUMAN PRESCRIPTION DRUG LABEL
Date: 20140310

ACTIVE INGREDIENTS: EPINEPHRINE 9 [hp_X]/1 mL; SUS SCROFA THYROID 9 [hp_X]/1 mL; INSULIN HUMAN 12 [hp_X]/1 mL; SUS SCROFA PITUITARY GLAND 12 [hp_C]/1 mL
INACTIVE INGREDIENTS: WATER; ALCOHOL

Drug Facts

ACTIVE INGREDIENTS:

Adrenalinum 9X, Thyroidinum (suis) 9X, Insulinum 12C, Pituitiaria glandula (suis) 12C.

RECOMMENDED USE:

Homeopathic medicine

CAUTION/RISK INFORMATION:

Consult a healthcare practitioner if symptoms persist or worsen or before use if you are pregnant or breastfeeding.

Keep out of reach of children.

Do not use if safety seal is broken.

KEEP OUT OF REACH OF CHILDREN.

RECOMMENDED DOSAGE:

Adults and adolescents, ages 12 and older: Take 8 drops under the tongue 3 times per day. Take 30 minutes before or after meals or as directed by your health practitioner. Consult a health care practitioner for prolonged use.

RECOMMENDED USE:

Homepathic medicine.

INACTIVE INGREDIENTS:

9% Ethanol (21 CFR 328.50), Glycerin, Purified Water.

QUESTIONS:

Life Choice C/O R4

PO Box 20380, Carson City, NV 89721

866-226-1722

Distributed by> Life Choice Ltd., Cochrane AB T4C 2S3

www.Lifechoice.net

PACKAGE LABEL DISPLAY

Life Choice

HgH+

Homeopathic Endocrine

Endocrine Homeopathique

DIN-HM: 80032688

30 ml (1 fl oz)